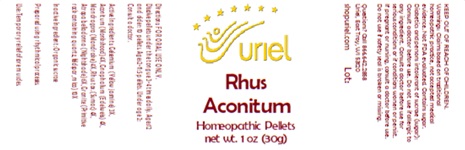 DRUG LABEL: Rhus Aconitum
NDC: 48951-8142 | Form: PELLET
Manufacturer: Uriel Pharmacy Inc.
Category: homeopathic | Type: HUMAN OTC DRUG LABEL
Date: 20250627

ACTIVE INGREDIENTS: GELSEMIUM SEMPERVIRENS ROOT 3 [hp_X]/1 1; ACONITUM NAPELLUS 4 [hp_X]/1 1; PSEUDOGNAPHALIUM LUTEOALBUM LEAF 4 [hp_X]/1 1; MANDRAGORA OFFICINARUM ROOT 4 [hp_X]/1 1; TOXICODENDRON PUBESCENS LEAF 4 [hp_X]/1 1; ATROPA BELLADONNA 6 [hp_X]/1 1; PENOXSULAM 10 [hp_X]/1 1
INACTIVE INGREDIENTS: SUCROSE

Rhus Aconitum

INDICATIONS AND USAGE

Directions: FOR ORAL USE ONLY.

DOSAGE AND ADMINISTRATION

Dissolve pellets under the tongue 3-4 times daily. Ages 12 and older: 10 pellets. Ages 2-11: 5 pellets. Under age 2: Consult a doctor.

ACTIVE INGREDIENT

Active Ingredients: Gelsemium (Yellow jasmine) 3X, Aconitum (Monkshood) 4X, Gnaphalium (Edelweiss) 4X, Mandragora (Mandrake) 4X, Rhus tox. (Sumac) 4X, Atropa belladonna (Nightshade) 6X, Granite (Primitive rock containing quartz, feldspar, mica) 10X

Inactive Ingredient: Sucrose

Prepared using rhythmical processes.

PURPOSE

Use: Temporary relief of sore muscles.

KEEP OUT OF REACH OF CHILDREN.

WARNINGS

Warnings: Claims based on traditional homeopathic practice, not accepted medical evidence. Not FDA evaluated. Contains sugar. Diabetics and persons intolerant of sucrose (sugar): Consult a doctor before use. Do not use if allergic to any ingredient. Consult a doctor before use for serious conditions or if conditions worsen or persist. If pregnant or nursing, consult a doctor before use. Do not use if safety seal is broken or missing.

Questions? Call 866.642.2858
Uriel, East Troy, WI 53120
shopuriel.com Lot: